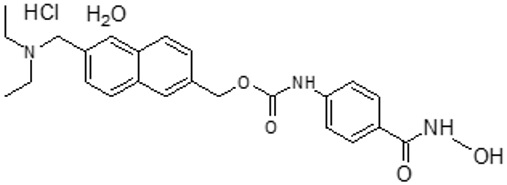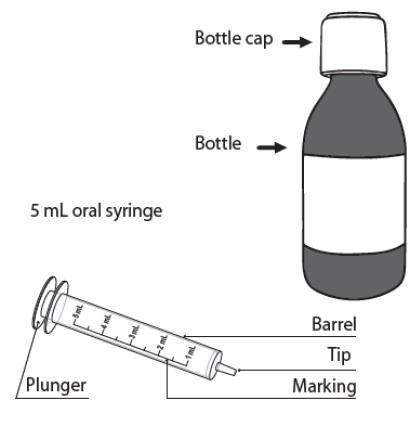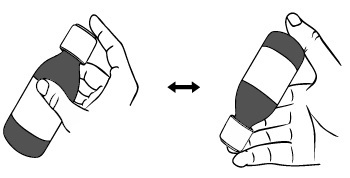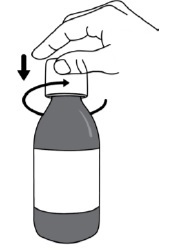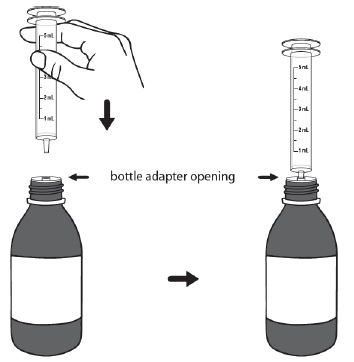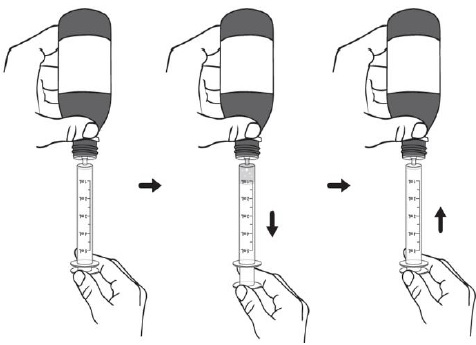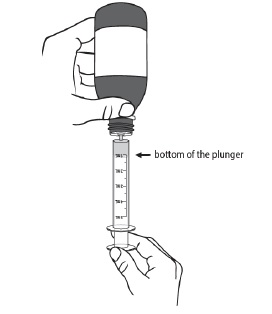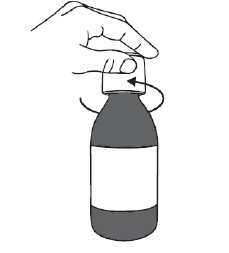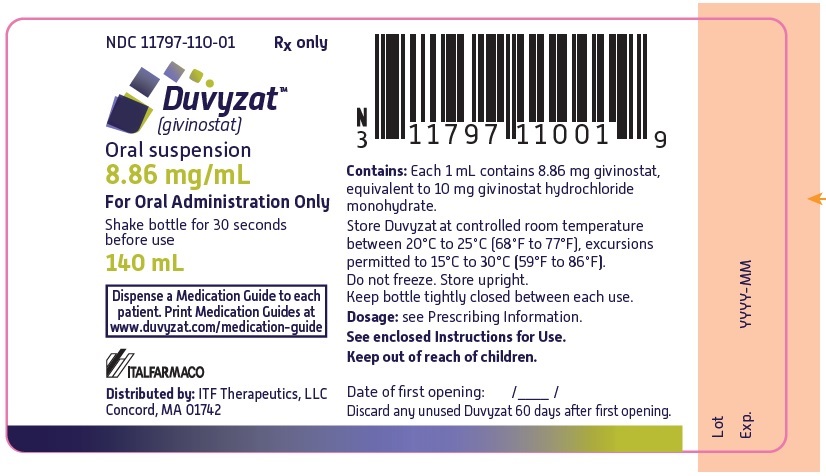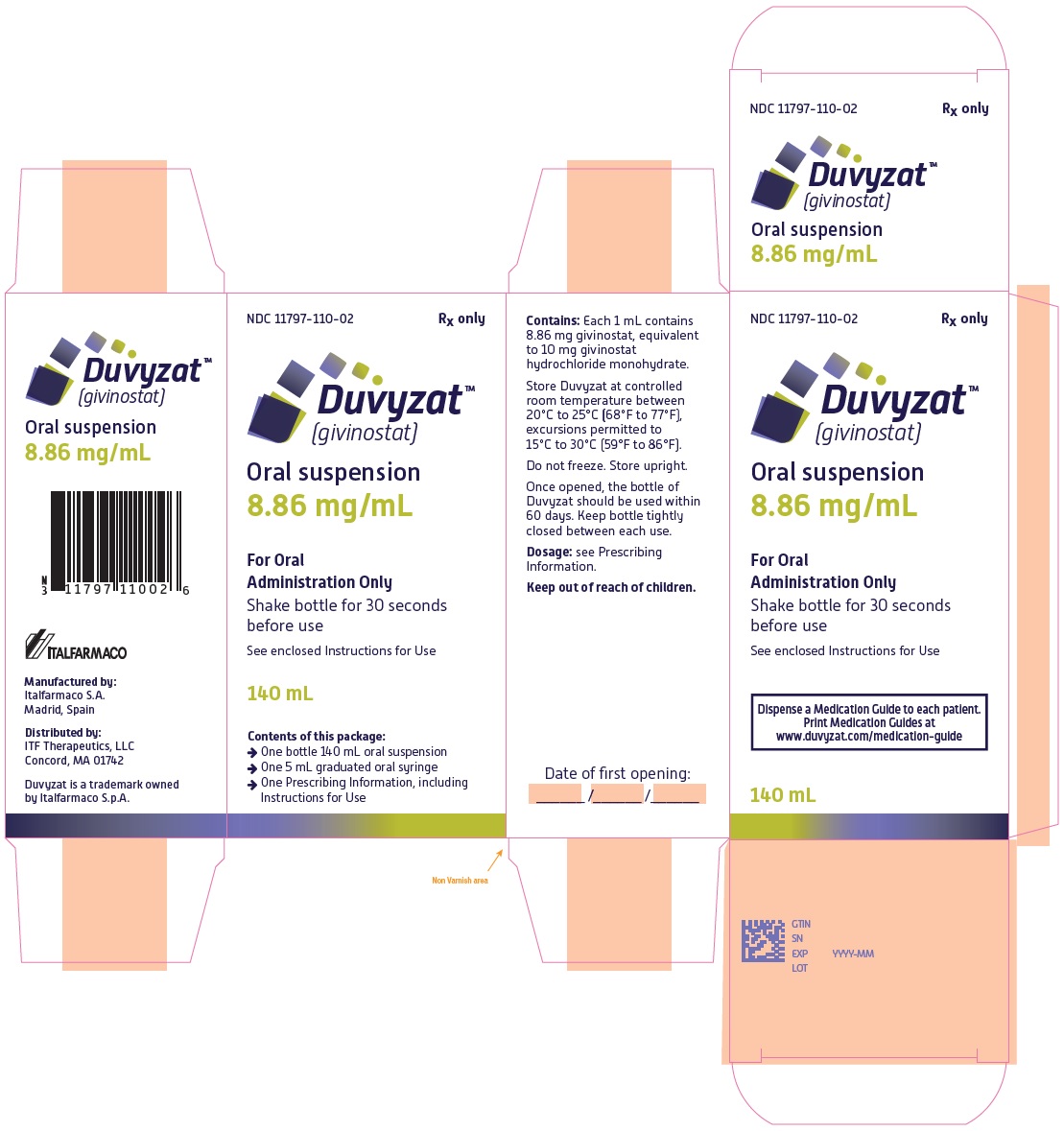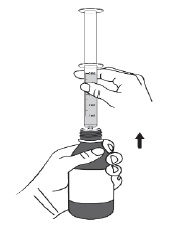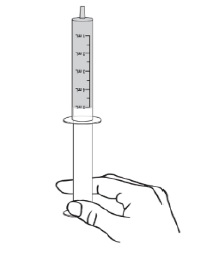 DRUG LABEL: DUVYZAT
NDC: 11797-110 | Form: SUSPENSION
Manufacturer: Italfarmaco SPA
Category: prescription | Type: HUMAN PRESCRIPTION DRUG LABEL
Date: 20241121

ACTIVE INGREDIENTS: GIVINOSTAT 8.86 mg/1 mL
INACTIVE INGREDIENTS: POLYSORBATE 20; GLYCERIN; TRAGACANTH; SODIUM BENZOATE; PEACH; COW MILK FAT; SACCHARIN SODIUM; NONCRYSTALLIZING SORBITOL SOLUTION; TARTARIC ACID; SODIUM HYDROXIDE; WATER

HIGHLIGHTS OF PRESCRIBING INFORMATION

These highlights do not include all the information needed to use DUVYZAT safely and effectively. See full prescribing information for DUVYZAT.
DUVYZAT (givinostat) oral suspension
Initial U.S. Approval: 2024

1 INDICATIONS AND USAGE

DUVYZAT is a histone deacetylase inhibitor indicated for the treatment of Duchenne muscular dystrophy (DMD) in patients 6 years of age and older. (1)

2 DOSAGE AND ADMINISTRATION

- Obtain and evaluate baseline platelet counts and triglycerides prior to initiation of DUVYZAT. Do not initiate DUVYZAT in patients with a platelet count less than 150 x 10^9/L. (2.1, 5.1, 5.2)
- The dosage of DUVYZAT is based on patient’s body weight. (2.2)
- Administer orally twice daily with food. (2.2)
- Dosage modifications may be needed for decreased platelet counts, diarrhea, increased triglycerides, or QTc prolongation. (2.3, 5.1, 5.2, 5.3, 5.4)

3 DOSAGE FORMS AND STRENGTHS

Oral suspension: 8.86 mg/mL givinostat. (3)

4 CONTRAINDICATIONS

None. (4)

5 WARNINGS AND PRECAUTIONS

- Hematological Changes: DUVYZAT can cause dose-related thrombocytopenia and other signs of myelosuppression, including anemia and neutropenia. Monitor platelets; dosage adjustment or discontinuation may be needed. (2.3, 5.1)
- Increased Triglycerides: An increase in triglycerides can occur; dosage modification may be needed. Discontinuation may be needed. (2.3, 5.2)
- Gastrointestinal Disturbances: Adjust dosage if moderate or severe diarrhea occurs. Antiemetics or antidiarrheal medications may be considered during treatment with DUVYZAT. Discontinue DUVYZAT if the symptoms persist. (2.3, 5.3)
- QTc Prolongation: Avoid use of DUVYZAT in patients who are at an increased risk for ventricular arrhythmias. (2.1, 5.4, 7.2)

6 ADVERSE REACTIONS

Most common adverse reactions (≥10% in DUVYZAT-treated patients) are diarrhea, abdominal pain, thrombocytopenia, nausea/vomiting, hypertriglyceridemia, and pyrexia. (6.1)

To report SUSPECTED ADVERSE REACTIONS, contact ITF Therapeutics, LLC. at 1-833-582-4312 or FDA at 1-800-FDA-1088 or www.fda.gov/medwatch.

7 DRUG INTERACTIONS

- Closely monitor when DUVYZAT is used in combination with an oral CYP3A4 sensitive substrate or a sensitive substrate of the OCT2 transporter, for which a small change in substrate plasma concentration may lead to serious toxicities. (7.1)
- Avoid concomitant use with other drugs that prolong the QTc interval; monitor ECG if concomitant use cannot be avoided. (7.2)

8 USE IN SPECIFIC POPULATIONS

- Pregnancy: Based on animal data, may cause fetal harm. (8.1)
- Hepatic Impairment: Exposure to givinostat is expected to be increased. (8.6)

FULL PRESCRIBING INFORMATION

1 INDICATIONS AND USAGE

DUVYZAT is indicated for the treatment of Duchenne muscular dystrophy (DMD) in patients 6 years of age and older.

2 DOSAGE AND ADMINISTRATION

2.1 Recommended Evaluation and Testing Before Initiation of DUVYZAT

Obtain and evaluate baseline platelet counts and triglycerides prior to initiation of DUVYZAT [see Warnings and Precautions (5.1, 5.2)]. Do not initiate DUVYZAT in patients with a platelet count less than 150 x 10^9/L. Monitor platelet counts and triglycerides as recommended during treatment to determine if dosage modifications are needed [see Dosage and Administration (2.3)].

In addition, in patients with underlying cardiac disease or taking concomitant medications that cause QT prolongation, obtain ECGs when initiating treatment with DUVYZAT, during concomitant use, and as clinically indicated [see Dosage and Administration (2.3), Warnings and Precautions (5.4), and Drug Interactions (7.2)].

2.2 Recommended Dosage

The recommended dosage of DUVYZAT is based on body weight and administered orally twice daily with food (see Table 1) [see Dosage and Administration (2.4)].

Table 1: Recommended Dosage in Patients 6 Years of Age and Older for the Treatment of DMD
Weight [Based on actual body weight] | Dosage | Oral Suspension Volume
10 kg to less than 20 kg | 22.2 mg twice daily | 2.5 mL twice daily
20 kg to less than 40 kg | 31 mg twice daily | 3.5 mL twice daily
40 kg to less than 60 kg | 44.3 mg twice daily | 5 mL twice daily
60 kg or more | 53.2 mg twice daily | 6 mL twice daily

2.3 Dosage Modifications for Adverse Reactions

Decrease in Platelets, Diarrhea, Increase in Triglycerides

DUVYZAT may cause adverse reactions [see Warnings and Precautions (5.1, 5.2, 5.3)], which may necessitate a dosage modification (see Table 2) if the following occur:

- Platelet count <150 x 10^9/L verified in two assessments one week apart
  or
- Moderate or severe diarrhea
  or
- Fasting triglycerides >300 mg/dL verified by two assessments one week apart

Based on the severity of these adverse reactions, treatment interruption prior to dosage modification should be considered.

Table 2: Dosage Modifications for Adverse Reactions in Patients 6 Years of Age and Older for the Treatment of DMD
 | First Dosage Modification [If the adverse reaction(s) persist after the first dosage modification, proceed to the second dosage modification.] |  | Second Dosage Modification [If the adverse reaction(s) persist after the second dosage modification, DUVYZAT should be discontinued.]
Weight [Based on actual body weight] | Dosage | Oral Suspension Volume | Dosage | Oral Suspension Volume
10 kg to less than 20 kg | 17.7 mg twice daily | 2 mL twice daily | 13.3 mg twice daily | 1.5 mL twice daily
20 kg to less than 40 kg | 22.2 mg twice daily | 2.5 mL twice daily | 17.7 mg twice daily | 2 mL twice daily
40 kg to less than 60 kg | 31 mg twice daily | 3.5 mL twice daily | 26.6 mg twice daily | 3 mL twice daily
60 kg or more | 39.9 mg twice daily | 4.5 mL twice daily | 35.4 mg twice daily | 4 mL twice daily

QTc Interval Prolongation

Withhold DUVYZAT if the QTc interval is > 500 ms or the change from baseline is > 60 ms [see Warnings and Precautions (5.4) and Drug Interactions (7.2)].

2.4 Preparation and Administration Instructions

See the Instructions for Use for further details.

- Before use, shake the DUVYZAT suspension for at least 30 seconds by inverting the bottle by 180°.
- Visually verify the homogeneity of the suspension.
- Using a graduated oral syringe, measure the appropriate volume of suspension corresponding to the prescribed dose of DUVYZAT.
- Administer orally with the provided graduated oral syringe.

2.5 Missed Dose

If a dose is missed, patients should not take double or extra doses.

3 DOSAGE FORMS AND STRENGTHS

Oral suspension: 8.86 mg/mL givinostat as a white to off-white or faintly pink, peach-cream flavored suspension.

4 CONTRAINDICATIONS

None.

5 WARNINGS AND PRECAUTIONS

5.1 Hematological Changes

DUVYZAT can cause dose-related thrombocytopenia and other signs of myelosuppression, including decreased hemoglobin and neutropenia.

In Study 1 [see Clinical Studies (14)], thrombocytopenia occurred in 33% of patients treated with DUVYZAT compared to no patients on placebo. The maximum decrease in platelets occurred within the first 2 months of therapy and remained low throughout the course of therapy. In a few patients, thrombocytopenia was associated with bleeding events including epistaxis, hematoma or contusions. Low platelet counts resulted in DUVYZAT dose reduction in 28% of patients. Patients with baseline platelet counts below the lower limit of normal were excluded from the study.

Decreased hemoglobin and decreased neutrophils were also observed in patients treated with DUVYZAT compared to placebo.

Monitor blood counts every 2 weeks for the first 2 months of treatment, at month 3, and then every 3 months thereafter. Modify the dosage of DUVYZAT for confirmed thrombocytopenia [see Dosage and Administration (2.3)]. Treatment should be permanently discontinued if the abnormalities worsen despite dose modification. If a patient develops signs or symptoms of thrombocytopenia, obtain a platelet count as soon as possible, and hold dosing until platelet count is confirmed.

5.2 Increased Triglycerides

DUVYZAT can cause elevations in triglycerides. In Study 1 [see Clinical Studies (14)], hypertriglyceridemia occurred in 23% of patients treated with DUVYZAT (one of whom had familial hypertriglyceridemia) compared to 7% of patients on placebo. High triglycerides (i.e., levels greater than 300 mg/dL) resulted in discontinuation and led to dosage modification in 2% and 8%, respectively, of patients treated with DUVYZAT.

Monitor triglycerides at 1 month, 3 months, 6 months, and then every 6 months thereafter. Modify the dosage if fasting triglycerides are verified > 300 mg/dL [see Dosage and Administration (2.3)]. Treatment with DUVYZAT should be discontinued if triglycerides remain elevated despite adequate dietary intervention and dosage adjustment.

5.3 Gastrointestinal Disturbances

Gastrointestinal disturbances, including diarrhea, nausea/vomiting, and abdominal pain were common adverse reactions in DUVYZAT clinical trials in DMD. In Study 1, diarrhea was reported in 37% of patients treated with DUVYZAT (with 1 severe case reported) compared to 20% of patients on placebo. Diarrhea usually occurred within the first few weeks of initiation of treatment with DUVYZAT.

Vomiting and nausea, sometimes severe and usually occurring within the first 2 months of treatment, occurred in 32% of patients treated with DUVYZAT compared to 18% of patients on placebo. Abdominal pain occurred in 34% of patients treated with DUVYZAT compared to 25% of patients on placebo. One case of abdominal pain was serious.

Antiemetics or antidiarrheal medications may be considered during treatment with DUVYZAT. Fluid and electrolytes should be replaced as needed to prevent dehydration [see Warnings and Precautions (5.4)]. Modify the dosage of DUVYZAT in patients with moderate or severe diarrhea, and treatment should be discontinued if significant symptoms persist [see Dosage and Administration (2.3)].

5.4 QTc Prolongation

DUVYZAT can cause prolongation of QTc interval [see Clinical Pharmacology (12.2)]. Avoid use of DUVYZAT in patients who are at an increased risk for ventricular arrhythmias (including torsades de pointes), such as those with congenital long QT syndrome, coronary artery disease, electrolyte disturbance [see Warnings and Precautions (5.3)], concomitant use of other medicinal products known to cause QT prolongation [see Drug Interactions (7.2)]. Obtain ECGs prior to initiating treatment with DUVYZAT in patients with underlying cardiac disease or in patients who are taking concomitant medications that cause QT prolongation [see Dosage and Administration (2.1)].

6 ADVERSE REACTIONS

The following clinically significant adverse reactions are described below and elsewhere in the labeling:

- Hematological Changes [see Warnings and Precautions (5.1)]
- Increased Triglycerides [see Warnings and Precautions (5.2)]
- Gastrointestinal Disturbances [see Warnings and Precautions (5.3)]
- QTc Prolongation [see Warnings and Precautions (5.4)]

6.1 Clinical Trials Experience

Because clinical trials are conducted under widely varying conditions, adverse reaction rates observed in the clinical trials of a drug cannot be directly compared to rates in the clinical trials of another drug and may not reflect the rates observed in practice.

In controlled and uncontrolled trials in patients with confirmed DMD, 222 male patients aged 6 years and older were treated with DUVYZAT, including 210 patients treated for ≥ 6 months, 187 patients for ≥ 12 months, and 105 patients for ≥ 24 months.

The safety profile of DUVYZAT is based on a double-blind, placebo-controlled, 18-month study in a total of 179 ambulant DMD patients aged 6 years or older on concomitant steroid treatment (Study 1) [see Clinical Studies (14)]. The dosage in Study 1 was weight-based [see Dosage and Administration (2.2)]. Patients were excluded from the study if they had the following abnormalities at the screening visit: platelet, white blood cell, or hemoglobin counts less than the lower limit of normal, triglycerides > 300 mg/dL (3.42 mmol/L) in fasting condition, or had a baseline-corrected QT interval, Fridericia’s correction (QTcF) of > 450 msec (mean of 3 consecutive readings 5 minutes apart) or a history of additional risk factors for torsades de pointes (e.g., heart failure, hypokalemia, or family history of long QT syndrome). Overall, 2% of the patients discontinued the study because of adverse reactions.

Adverse reactions reported in >5% of DUVYZAT-treated patients at a frequency at least 5% greater than that of the placebo group are presented in Table 3 below.

Table 3. Adverse Reactions Reported in >5% of DUVYZAT-Treated Patients and at Least 5% Greater than Placebo in Study 1
Adverse Reaction | DUVYZAT N=118 % | Placebo N=61 %
Diarrhea | 37 | 20
Abdominal pain | 34 | 25
Thrombocytopenia [Thrombocytopenia includes platelet count decreased and thrombocytopenia] | 33 | 0
Nausea/Vomiting | 32 | 18
Hypertriglyceridemia | 23 | 7
Pyrexia | 13 | 8
Myalgia | 9 | 3
Rash | 9 | 2
Arthralgia | 8 | 2
Fatigue | 8 | 0
Constipation | 7 | 2
Decreased appetite | 7 | 0

Less Common Adverse Reactions in Study 1

Adverse reactions of hypothyroidism and/or thyroid stimulating hormone (TSH) increased occurred in 5% of patients treated with DUVYZAT compared to 2% of patients who received placebo.

7 DRUG INTERACTIONS

7.1 Effect of DUVYZAT on Other Drugs

CYP3A4 Sensitive Substrates

Givinostat is a weak intestinal CYP3A4 inhibitor [see Clinical Pharmacology (12.3)]. Closely monitor when DUVYZAT is used in combination with orally administered CYP3A4 sensitive substrates for which a small change in substrate plasma concentration may lead to serious toxicities.

OCT2 Sensitive Substrates

Givinostat is a weak inhibitor of the renal uptake transporter OCT2 [see Clinical Pharmacology (12.3)]. Closely monitor when DUVYZAT is used in combination with drugs known as a sensitive substrate of the OCT2 transporter for which a small change in substrate plasma concentration may lead to serious toxicities.

7.2 Effect of Other Drugs on DUVYZAT

Drugs that Prolong the QTc Interval

Avoid concomitant use of DUVYZAT with other product(s) with a known potential to prolong the QTc interval. If concomitant use cannot be avoided, obtain ECGs when initiating, during concomitant use, and as clinically indicated [see Warnings and Precautions (5.4)]. Withhold DUVYZAT if the QTc interval is > 500 ms or the change from baseline is > 60 ms [see Dosage and Administration (2.1)].

DUVYZAT causes QTc interval prolongation [see Clinical Pharmacology (12.2)]. Concomitant use of DUVYZAT with other products that prolong the QTc interval may result in a greater increase in the QTc interval and adverse reactions associated with QTc interval prolongation, including Torsade de pointes, other serious arrythmias, and sudden death [see Warnings and Precautions (5.4)].

8 USE IN SPECIFIC POPULATIONS

8.1 Pregnancy

Risk Summary

DUVYZAT is indicated for the treatment of DMD, which is a disease of predominantly young male patients. Therefore, there are no adequate data available to assess the use of DUVYZAT in pregnant women. In animal studies, oral administration of givinostat during organogenesis resulted in decreased fetal body weight and increased structural variations; oral administration during pregnancy and lactation resulted in increased embryofetal and offspring mortality and neurobehavioral changes in the offspring. In the U.S. general population, the estimated background risk of major birth defects and miscarriage in clinically recognized pregnancies is 2-4% and 15-20%, respectively.

Data

Animal Data

Oral administration of givinostat (0, 40, 80, or 160 mg/kg/day) to pregnant rats throughout organogenesis resulted in reduced fetal body weight at the highest dose tested and increases in the incidence of skeletal and visceral variations at the mid and high doses. The no-effect dose (40 mg/kg/day) for adverse effects on embryofetal development was associated with maternal plasma exposures (AUC) lower than that in humans at the maximum recommended human dose (MRHD) of 53.2 mg twice daily.

Oral administration of givinostat (0, 40, 80, or 160 mg/kg/day) to pregnant rabbits throughout organogenesis resulted in maternal death at the highest dose tested, resulting in too few fetuses to evaluate. No adverse effects on embryofetal development were observed at the low and mid doses. Plasma exposures (AUC) at the higher no-effect dose (80 mg/kg) for adverse effects on embryofetal development were approximately 4 times that in humans at the MRHD.

Oral administration of givinostat (0, 40, 80, or 160 mg/kg/day) to rats throughout pregnancy and lactation resulted in increases in embryofetal mortality, stillbirths, and offspring mortality at the highest dose tested. When offspring were tested postweaning (postnatal day 49), adverse effects on behavior (decreased open field activity) were observed at all doses. A no-effect dose for adverse developmental effects was not identified; plasma exposures (AUC) at the lowest dose tested were lower than that in humans at the MRHD.

8.2 Lactation

Risk Summary

There are no human or animal data to assess the effect of DUVYZAT or its metabolites on milk production, the presence of givinostat in milk, or the effects on the breastfed infant. The developmental and health benefits of breastfeeding should be considered along with the mother's clinical need for DUVYZAT and any potential adverse effects on the breastfed infant from DUVYZAT or from the underlying maternal condition.

8.3 Females and Males of Reproductive Potential

No human data are available on the effect of DUVYZAT on reproductive potential.

Animal studies indicate possible adverse effects on reproduction [see Nonclinical Toxicology (13.1)].

8.4 Pediatric Use

The safety and effectiveness of DUVYZAT in children aged 6 years and older have been established [see Clinical Studies (14)]. Safety and effectiveness in pediatric patients below the age of 6 years have not been established.

Juvenile Animal Data

In a study in juvenile male and female rats, givinostat was orally administered at doses of 0, 10, 20, or 40 mg/kg on postnatal days (PND) 7 to 27, doses of 0, 15, 30, or 60 mg/kg/day on PNDs 28 to 48, and doses of 0, 15, 45, or 90 mg/kg/day on PNDs 49 to 92. Adverse effects on behavior (increased locomotor activity and decreased auditory startle prepulse inhibition) were observed at the high dose at the end of the dosing period. Adverse effects on locomotor activity, but not prepulse inhibition, were observed at the end of the recovery period primarily at the mid and high doses. Persistent decreases in bone density were observed at all doses tested. A no-effect dose for adverse effects on postnatal development was not identified; the lowest dose tested was associated with plasma exposures (AUC) less than that in humans at the MRHD.

8.5 Geriatric Use

DMD is largely a disease of children and young adults; therefore, there is no experience with DUVYZAT in geriatric DMD patients.

8.6 Hepatic Impairment

A dedicated clinical study was not conducted to evaluate the pharmacokinetics of DUVYZAT in subjects with hepatic impairment, and no recommendation for dosage adjustment can be made for patients with hepatic impairment. Because DUVYZAT is eliminated mainly through hepatic metabolism, hepatic impairment is expected to increase the exposure of givinostat [see Clinical Pharmacology (12.3)].

11 DESCRIPTION

DUVYZAT (givinostat) oral suspension contains givinostat hydrochloride monohydrate, a histone deacetylase inhibitor. Givinostat hydrochloride monohydrate is designated chemically as: [6-(diethylaminomethyl)naphthalen-2-yl]methyl[4(hydroxycarbamoyl) phenyl] carbamate hydrochloride monohydrate. The molecular formula is C24H27N3O4•HCl•H2O and the molecular weight is 475.97 g/mol. Its structural formula is:

Givinostat hydrochloride monohydrate is a white to off-white, non-hygroscopic, crystalline powder that is very slightly to slightly soluble in aqueous media and slightly soluble in ethanol.

DUVYZAT contains givinostat 8.86 mg/mL (equivalent to givinostat hydrochloride monohydrate 10 mg/mL) and the following inactive ingredients: cream flavor, glycerin, non-crystallizing sorbitol solution, peach flavor, polysorbate 20, purified water, saccharin sodium, sodium benzoate, sodium hydroxide, tartaric acid, and tragacanth.

12 CLINICAL PHARMACOLOGY

12.1 Mechanism of Action

DUVYZAT is a histone deacetylase inhibitor. The precise mechanism by which DUVYZAT exerts its effect in patients with DMD is unknown.

12.2 Pharmacodynamics

Muscle Fat Fraction as Assessed by MR Spectroscopy

The percentage of fat fraction present in the vastus lateralis muscles (VLM) of the thigh was measured in Study 1 [see Clinical Studies (14)] using magnetic resonance spectroscopy. At 18 months, for the patients with VLM fat fraction baseline in the range of >5% to ≤30%, a mean increase (absolute difference from baseline levels) of VLM fat fraction was 7.48% in the DUVYZAT-treated patients compared to a 10.89% increase in patients who received placebo.

Cardiac Electrophysiology

The largest mean increase in QTc interval of 13.6 ms (upper confidence interval of 17.1 ms) occurred 5 hours after administration of givinostat 265.8 mg to healthy subjects (approximately 5 times the 53.2 mg dose recommended for DMD patients weighing 60 kg or more) [see Warnings and Precautions (5.4)].

12.3 Pharmacokinetics

Givinostat exhibits linear kinetics with the studied dose range. Systemic exposure to givinostat was dose-proportional across the therapeutic dose range. Steady-state concentrations are achieved within 5 to 7 days after twice daily dosing. An accumulation of less than 2-fold was observed for givinostat after twice daily administration.

Absorption

Absolute bioavailability was not determined. The time to maximum plasma concentrations is about 2 to 3 hours after oral administration.

Effect of Food

A high fat standard meal resulted in an increase in the exposure (about 40% increase in area under the plasma concentration-time curve [AUC] and about 23% increase in maximum plasma concentration [Cmax]) and a delay in time to maximum concentration (Tmax) from 2 to 3 hours [see Dosage and Administration (2.2)].

Distribution

Givinostat is approximately 96% bound to human plasma proteins and is slightly partitioned into red blood cells (blood to plasma ratio = 1.3).

Elimination

In plasma, apparent elimination half-life of givinostat is about 6 hours.

Metabolism

In vitro studies with human enzymatic preparations together with animal metabolism showed that givinostat is extensively metabolized forming several metabolites. CYP450 and UGTs are not involved in the main metabolic reactions. Four major metabolites, which are not active with respect to the efficacy of givinostat, have been characterized in humans and preclinical species.

Excretion

The elimination of givinostat is likely dependent on metabolism followed by renal and biliary excretion of the resulting metabolites as suggested by the mass balance study in the rat. Urinary excretion of givinostat in humans is minimal (<3% of the dose).

Specific Populations

The population PK analyses show that the PK of givinostat can be affected by body weight, while age has no effects on the pharmacokinetics of givinostat.

Patients with Hepatic Impairment

The pharmacokinetics and safety of givinostat have not been studied in patients with hepatic impairment. Givinostat is highly metabolized and therefore the impact of hepatic impairment on the exposure of givinostat cannot be excluded [see Use in Specific Populations (8.6)].

Patients with Renal Impairment

The pharmacokinetics and safety of givinostat have not been studied in patients with renal impairment. However, renal impairment is not expected to impact the exposure of givinostat because renal excretion is not a significant route of givinostat elimination.

Drug Interaction Studies

In Vitro

Givinostat is not a substrate of cytochrome P450 (CYP450) enzymes and uridine diphosphate glucuronosyltransferase (UGT). Therefore, coadministration of drugs that are inducers or inhibitors of major metabolizing enzymes will not significantly affect the systemic exposure of givinostat.

Givinostat and its metabolites ITF2374, ITF2375, ITF2440, and ITF2563 were investigated as inhibitors of the main CYP450 subfamilies, and the results indicated no inhibition is expected of CYP1A2, 2C9, 2C19, 2D6, 2B6, 2C8, and 3A4. Givinostat showed induction of CYP1A2, 2B6, and CYP3A4.

In vitro studies indicate that givinostat is a substrate of the intestinal transporters: P-glycoprotein (P-gp) and breast cancer resistance protein (BCRP). Givinostat showed the potential to inhibit the intestinal transporter P-gp (MDR1) and BCRP based on in vitro results. However, these interactions are not expected to be clinically meaningful.

In Vivo

A weak inhibition of the renal uptake transporter OCT2 by givinostat was seen in clinical trials by creatinine (OCT2 substate) measurements [see Drug Interactions (7.1)].

A clinical drug interaction study was conducted in healthy volunteers to assess the effects of coadministration of givinostat with other drugs and results indicated that:

- givinostat has a weak inhibition of the intestinal CYP3A4 enzyme based on the exposure of a CYP3A4 substrate, midazolam, [see Drug Interactions (7.1)]
- givinostat does not likely inhibit P-gp transporters based on the exposure of dabigatran
- strong P-gp inhibitors have a weak effect on givinostat based on exposure of clarithromycin, which had an increase in Cmax by about 40% without a significant change of AUC.

The effect of BCRP inhibitors on givinostat PK was not studied in a clinical study. However, the effect of BCRP inhibitors on givinostat PK is expected to be smaller than P-gp inhibitors based on the comparison of the two transporters mediated efflux ratios determined in the in vitro cell models.

13 NONCLINICAL TOXICOLOGY

13.1 Carcinogenesis, Mutagenesis, Impairment of Fertility

Carcinogenesis

Studies to assess the carcinogenic potential of givinostat have not been conducted.

Mutagenesis

Givinostat was positive in a bacterial reverse mutation (Ames) assay, and negative in an in vitro mammalian cell (mouse lymphoma) mutation assay, an in vitro chromosomal aberration assay in mammalian (human lymphocytes) cells, and an in vivo gene mutation assay (with Pig-a endpoints) in Big Blue transgenic rats.

Impairment of Fertility

Oral administration of givinostat (0, 40, 80, or 160 mg/kg) prior to and throughout mating in male and female rats and continuing to gestation day 7 in females, resulted in no adverse effects on fertility. However, there was an increase in corpora lutea at the mid and high doses and increased pre- and postimplantation loss at all doses. A no-effect dose for adverse effects on early embryonic development was not identified; plasma exposures (AUC) at the lowest dose tested were lower than that in humans at the maximum recommended human dose of 53.2 mg twice daily.

14 CLINICAL STUDIES

The effectiveness of DUVYZAT for the treatment of Duchenne muscular dystrophy (DMD) was evaluated in a randomized, double-blind, placebo-controlled 18-month study (Study 1; NCT02851797). A total of 179 patients were randomized 2:1 to receive either DUVYZAT (n = 118) or placebo (n = 61). A weight-based dose regimen was applied [see Dosage and Administration (2.2)]. The study included male patients 6 years of age and older with a confirmed diagnosis of DMD who were ambulatory and on a stable dosage of corticosteroids. At baseline, patients had a mean age of 9.8 years, 90% were White, 3% were Asian, 3% were Black.

The primary endpoint was the change from baseline to Month 18 in 4-stair climb (4SC) time for DUVYZAT compared to placebo. The 4SC is a measure of muscle function that tests the time it takes to climb 4 stairs. A secondary efficacy endpoint was change from baseline to Month 18 in physical function as assessed by the North Star Ambulatory Assessment (NSAA).

The primary analysis population was based on a prespecified range of baseline muscle fat fraction as determined by MR spectroscopy. Patients treated with DUVYZAT showed statistically significant less decline in the 4-stair climb compared to placebo (see Table 4). Patients treated with givinostat experienced less worsening on the NSAA compared to placebo, which was nominally significant but not statistically significant based on the prespecified multiplicity adjustment.

Table 4. Change from Baseline to Month 18 on 4SC Compared to Placebo [Givinostat or placebo were administered in addition to a stable dose of corticosteroids throughout the study]
 | Mean Baseline 4SC (seconds) | Mean Change from Baseline | Treatment Difference from Placebo (95% CI) | p-value
DUVYZAT (n = 81) | 3.39 | 1.25 | -1.78 (-3.46, -0.11) | 0.037
Placebo (n = 39) | 3.48 | 3.03 | -1.78 (-3.46, -0.11) | 0.037

16 HOW SUPPLIED/STORAGE AND HANDLING

16.1 How Supplied

DUVYZAT (givinostat) oral suspension is a white to off-white or faintly pink, peach-cream flavored suspension. It is supplied in an amber polyethylene terephthalate bottle closed with a high-density polyethylene child-resistant, screw cap with low-density polyethylene syringe adapter, containing 140 mL of oral suspension (NDC 11797-110-01). Each mL contains 8.86 mg of givinostat.

DUVYZAT is supplied in a carton, NDC 11797-110-02, containing:

- one bottle containing 140 mL oral suspension
- one 5 mL graduated oral syringe
- Prescribing Information and Instructions for Use

The Medication Guide is available at www.duvyzat.com/medication-guide.

16.2 Storage and Handling

Store at 20°C to 25°C (68°F to 77°F), excursions permitted to 15°C to 30°C (59°F to 86°F) [see USP Controlled Room Temperature]. Do not freeze. Store upright.

Discard any unused DUVYZAT remaining after 60 days of first opening of the bottle.

17 PATIENT COUNSELING INFORMATION

Advise the patient to read the FDA-approved patient labeling (Medication Guide and Instructions for Use).

Administration Instructions

Instruct patients or caregivers to [see Dosage and Administration (2.4)]:

- Shake DUVYZAT oral suspension well before measuring out each dose.
- Administer using the provided graduated oral syringe to measure the appropriate volume of suspension corresponding to the prescribed dose for the patient.
- Take DUVYZAT with food.
- Discard any unused DUVYZAT oral suspension remaining after 60 days of first opening the bottle.

Hematological Changes

Inform patients and/or caregivers that DUVYZAT can cause hematological changes including a decrease in platelet counts (thrombocytopenia), anemia, and a decrease in neutrophils (neutropenia) [see Warnings and Precautions (5.1)]. Advise patients to notify their healthcare provider if they have any signs or symptoms of these adverse reactions (e.g., easy bruising, excessive bleeding from cuts, blood in the stool, fatigue). Instruct patients to adhere to the testing recommended to monitor for these adverse reactions. Inform patients that their dosage may need to be changed or their treatment may need to be stopped depending on the results of their test for platelet counts.

Increased Triglycerides

Inform patients and/or caregivers that DUVYZAT can cause an increase in triglycerides, [see Warnings and Precautions (5.2)]. Instruct patients to adhere to the testing recommended to monitor for this adverse reaction. Inform patients that their dosage may need to be changed or their treatment may need to be stopped depending on the results of their test for triglycerides.

Gastrointestinal Disturbances

Inform patients and/or caregivers that DUVYZAT can cause diarrhea and vomiting, which may require medication for treatment [see Warnings and Precautions (5.3)]. Advise patients to maintain hydration if diarrhea or vomiting occurs and contact their healthcare provider if the symptoms persist or become moderate to severe. Inform patients that their dosage may need to be changed or their treatment may need to be stopped depending on the severity of diarrhea.

QTc Prolongation

Inform patients and/or caregivers that DUVYZAT can cause prolongation of the QTc interval [see Warnings and Precautions (5.4)]. Instruct patients to notify their healthcare provider if they have or develop any symptoms of significant QTc prolongation (e.g., dizziness, lightheadedness, syncope) or new cardiac issues and before taking any over-the-counter (e.g., diphenhydramine), herbal (e.g., echinacea), or prescription medications (e.g., antibiotics).

Manufactured by:
Italfarmaco S.A.
Madrid, Spain

Distributed by:
ITF Therapeutics, LLC
Concord, MA 01742

DUVYZAT is a trademark owned by Italfarmaco S.p.A.

All rights reserved.

MEDICATION GUIDE
DUVYZAT™ (doo' vi zat)
(givinostat)
oral suspension

What is the most important information I should know about DUVYZAT?
DUVYZAT can cause serious side effects including:

- Low platelet counts in your blood (thrombocytopenia). Platelets are important for blood clotting, and a decrease in their numbers can lead to an increased risk of bleeding or bruising. Your healthcare provider will check your blood count before you start DUVYZAT and regularly during treatment for any signs of thrombocytopenia. Call your healthcare provider right away if you notice any unusual bleeding or small red or purple spots on the skin called petechiae. Your healthcare provider may change your dose of DUVYZAT if your blood platelet counts continue to be low or may stop your treatment with DUVYZAT.
- Increased levels of fat (triglycerides) in your blood. You may not have any symptoms, so your healthcare provider will do blood tests before you start DUVYZAT and regularly during treatment to check your triglyceride levels. Your healthcare provider may change your dose of DUVYZAT if your triglyceride levels continue to be high or may stop your treatment with DUVYZAT.
- Frequent watery loose stools (diarrhea) and vomiting. DUVYZAT can cause vomiting and moderate to severe diarrhea. If diarrhea occurs, you should keep track of the frequency and severity of your diarrhea symptoms, drink plenty of fluids, and contact your healthcare provider. Your healthcare provider may change your dose of DUVYZAT if the diarrhea cannot be managed or does not go away. Your healthcare provider may also stop your treatment with DUVYZAT.

What is DUVYZAT?
DUVYZAT is a prescription medicine that is used for the treatment of Duchenne muscular dystrophy (DMD) in people 6 years of age and older.
It is not known if DUVYZAT is safe and effective in children under 6 years of age.

Before taking DUVYZAT, tell your healthcare provider about all of your medical conditions, including if you:

- have any heart problems or if you take any medicines that could increase your chance for irregular heart rhythms.
- have any bleeding problems.

Tell your healthcare provider about all of the medicines you take, including prescription and over-the-counter medicines, vitamins, and herbal supplements.
Taking DUVYZAT with certain other medicines may affect each other. Taking DUVYZAT with other medicines can cause serious side effects. Do not start or stop other medicines without talking to your healthcare provider.
Know the medicines you take. Keep a list of them to show your healthcare provider and pharmacist when you get a new medicine.

How should I take DUVYZAT?

- See the Instructions for Use that came with your DUVYZAT medicine for detailed instructions on how to take DUVYZAT the right way.
- Take DUVYZAT by mouth with food.
- Take DUVYZAT exactly as prescribed. Your healthcare provider will tell you how much DUVYZAT to take and when to take it.
- Your healthcare provider may change your dose of DUVYZAT if needed. Do not change your dose of DUVYZAT without talking to your healthcare provider.
- Shake the bottle for at least 30 seconds by continuously turning the bottle up and down. Stop when the DUVYZAT suspension looks the same throughout.
- Take the prescribed dose of DUVYZAT by mouth (orally) using the oral syringe that came with your DUVYZAT medicine. Do not throw away the oral syringe.
- DUVYZAT should not be mixed with water or other liquids.
- If you miss a dose of DUVYZAT, skip the missed dose and take your next dose of DUVYZAT as scheduled.

What are the possible side effects of DUVYZAT?
DUVYZAT can cause serious side effects, including:

- see “What is the most important information I should know about DUVYZAT?”
- changes in the electrical activity of your heart called QT Prolongation. QT Prolongation can increase the risk of developing a type of irregular heart rhythm known as Torsades de Pointes. Call your healthcare provider right away if you feel faint, have an irregular heartbeat, feel dizzy, or lose consciousness.

The most common side effects of DUVYZAT include:

- loose, watery stools (diarrhea)
- nausea
- vomiting
- stomach (abdominal) pain

- low platelet counts in the blood
- increased fat levels in the blood
- fever

Tell your healthcare provider if you have any side effect that bothers you or that does not go away.
These are not all of the possible side effects of DUVYZAT. For more information, ask your healthcare provider or pharmacist.
Call your doctor for medical advice about side effects. You may report side effects to FDA at 1-800-FDA-1088.

General information about the safe and effective use of DUVYZAT.
Medicines are sometimes prescribed for purposes other than those listed in a Medication Guide. Do not use DUVYZAT for a condition for which it was not prescribed. Do not give DUVYZAT to other people, even if they have the same symptoms that you have. It may harm them.
You can ask your pharmacist or healthcare provider for information about DUVYZAT that is written for healthcare professionals.

What are the ingredients in DUVYZAT?

Active ingredient: givinostat

Inactive ingredients: cream flavor, glycerin, non-crystallizing sorbitol solution, peach flavor, polysorbate 20, purified water, saccharin sodium, sodium benzoate, sodium hydroxide, tartaric acid, and tragacanth.

Distributed by:
ITF Therapeutics, LLC
Concord, MA 01742
For more information, go to www.DUVYZAT.com or call 1-833-582-4312

This Medication Guide has been approved by the U.S. Food and Drug Administration.

Issued: 3/2024

PATIENT INFORMATION

INSTRUCTIONS FOR USE
DUVYZAT [doo' vi zat]
(givinostat)
oral suspension

This Instructions for Use contains information on how to take DUVYZAT. Ask your healthcare provider or pharmacist if you have any questions on how to take DUVYZAT.

Each DUVYZAT carton contains (see Figure A):

- 1 (one) bottle of 140 mL oral suspension
- 1 (one) 5 mL oral syringe

Figure A

Important information you need to know before you take DUVYZAT:

- Keep these instructions for future use.
- Do not share DUVYZAT with anyone else.
- Do not mix DUVYZAT with water or other liquids.
- Ask your healthcare provider or pharmacist to show you how to measure your prescribed dose.
- Do not throw away the oral syringe. Always use the oral syringe that comes with DUVYZAT to measure your prescribed dose.
- Use the medicine in the bottle within 60 days after you first open it. Throw away any unused DUVYZAT remaining in this bottle after 60 days. Write the date you open the bottle on the bottle label.

How to take DUVYZAT:

- Take DUVYZAT exactly as prescribed by your healthcare provider.
- Take DUVYZAT by mouth (orally) 2 times each day.
- The dose of DUVYZAT is based on how much you weigh.
- Take DUVYZAT with food.
- Take DUVYZAT using the oral syringe that comes with DUVYZAT.

Remove the DUVYZAT bottle and the oral syringe from the carton (see Figure A above).

Step 1. Make sure the bottle is closed properly and shake the bottle for at least 30 seconds by continuously turning the bottle up and down (see Figure B). Stop when the DUVYZAT oral suspension is mixed well and looks the same throughout.

Figure B

Step 2. Open the bottle by pressing down on the bottle cap and turning it to the left (counter-clockwise) (see Figure C). Do not throw away the bottle cap.

Figure C

Step 3.
For first time use only: Take the provided oral syringe to be used and firmly insert the tip of the oral syringe into the bottle adapter opening (see Figure D).
For all other uses: Take the provided oral syringe to be used, push the plunger all the way down (to remove the air) and firmly insert the tip of the oral syringe into the bottle adapter opening (see Figure D).

Figure D

Step 4. While holding the oral syringe in place, turn the bottle upside down. Slowly pull the plunger down to pull back a small amount of the suspension. Then push the plunger all the way up to remove any air bubbles (see Figure E).

Figure E

Step 5. Slowly pull the plunger down until the bottom of the plunger is even with the markings on the oral syringe for the prescribed dose of DUVYZAT (see Figure F). If your prescribed dose is more than 5 mL, you will need to use the same oral syringe more than one time.

Figure F

Step 6. While keeping the plunger in the same position, turn the bottle upright, and place it carefully on a flat surface. Remove the oral syringe by gently twisting or pulling it out from the bottle adapter opening. Do not hold the oral syringe by the plunger because the plunger may come out (see Figure G).
Take or give DUVYZAT right away after it is drawn up into the oral syringe. Do not store the filled oral syringe.

Figure G

Step 7. Check that the prescribed volume (mL) of DUVYZAT has been drawn up into the oral syringe (see Figure H). Figure H shows an example of a 5 mL dose. Your dose may be a different volume.

Figure H

Step 8. The child or adult should sit upright to take a dose of DUVYZAT. Place the tip of the oral syringe against the inside of the cheek. Slowly push the plunger all the way down until there is no more medicine left in the oral syringe.
If your prescribed dose is more than 5 mL, repeat Step 3 through Step 8 to give the remaining part of the dose.

Step 9. After use, replace the bottle cap and turn the bottle cap to the right (clockwise) to close the bottle (see Figure I).

Figure I

Step 10. Wash the oral syringe in water and allow to dry.

Keep the oral syringe for use with this bottle of DUVYZAT. Store the oral syringe in a clean, dry place.

How to store DUVYZAT:

- Store DUVYZAT at room temperature between 68°F to 77°F (20°C to 25°C).
- Do not freeze DUVYZAT.
- Store DUVYZAT upright.
- After opening the bottle of DUVYZAT, use within 60 days. Throw away (dispose of) any DUVYZAT that is not used within 60 days after opening the bottle. Ask your pharmacist how to properly throw away (dispose of) medicines you no longer use.
- Do not use DUVYZAT after the expiration date (EXP) on the carton and the bottle. The expiration date is the last day of the expiration month.
- Keep the bottle tightly closed between each use.
- Keep DUVYZAT and all medicines out of the sight and reach of children.

This Instructions for Use has been approved by the U.S. Food and Drug Administration.
Approved: 3/2024

Manufactured by:
Italfarmaco S.A.
Madrid, Spain

Distributed by:
ITF Therapeutics, LLC
Concord, MA 01742

DUVYZAT is a trademark owned by Italfarmaco S.p.A

All rights reserved.

PRINCIPAL DISPLAY PANEL

NDC 11797-110-01

Rx only

DuvyzatTM
[givinostat]
Oral suspension
8.86 mg/mL

For Oral Administration Only
Shake bottle for 30 seconds
before use

140 mL

Dispense a Medication Guide to each
patient. Print Medication Guides at
www.duvyzat.com/medication-guide

ITALFARMACO

Distributed by: ITF Therapeutics, LLC
Concord, MA 01742

PRINCIPAL DISPLAY PANEL

NDC 11797-110-02

Rx only

DuvyzatTM
[givinostat]
Oral suspension
8.86 mg/mL

For Oral
Administration Only
Shake bottle for 30 seconds
before use

See enclosed Instructions for Use

Dispense a Medication Guide to each patient.
Print Medication Guides at
www.duvyzat.com/medication-guide

140 mL